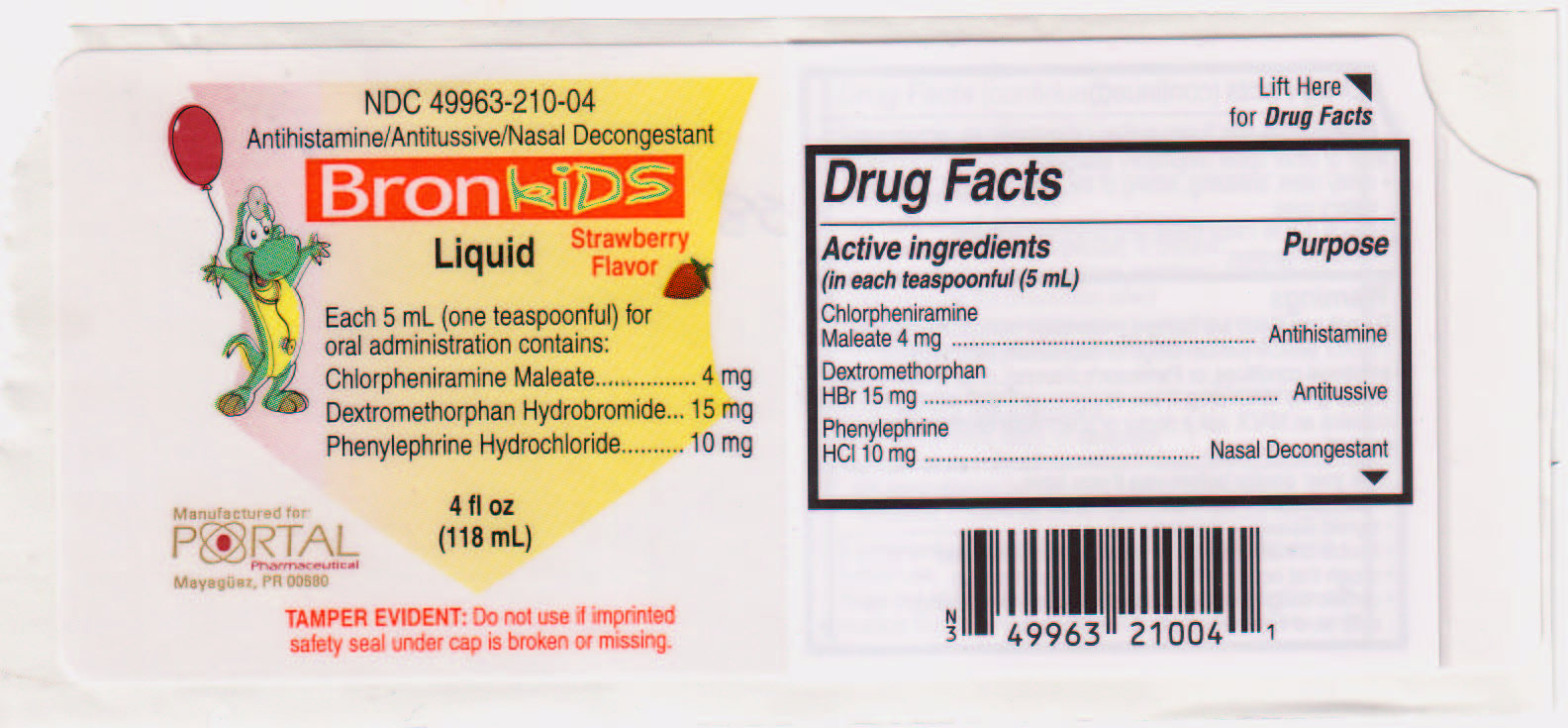 DRUG LABEL: Bronkids
NDC: 49963-210 | Form: LIQUID
Manufacturer: Portal Pharmaceutical
Category: otc | Type: HUMAN OTC DRUG LABEL
Date: 20100104

ACTIVE INGREDIENTS: CHLORPHENIRAMINE MALEATE 4 mg/5 mL; DEXTROMETHORPHAN HYDROBROMIDE 15 mg/5 mL; PHENYLEPHRINE HYDROCHLORIDE 10 mg/5 mL
INACTIVE INGREDIENTS: FD&C RED NO. 40; GLYCERIN; PROPYLENE GLYCOL; WATER; SACCHARIN SODIUM; SORBITOL

Drug Facts

Active ingredients Purpose
(in each teaspoonful (5 mL)
Chlorpheniramine
Maleate 4 mg ...................................................... Antihistamine
Dextromethorphan
HBr 15 mg ............................................................... Antitussive
Phenylephrine
HCl 10 mg ................................................. Nasal Decongestant

Do not use if you are taking a prescription monoamine oxidase inhibitor (MAOI), (certain drugs for depression, psychiatric or emotional conditions, or Parkinson's disease) or for two weeks after stopping the MAOI drug. If you do not know if your prescription drug contains an MAOI, ask a doctor or pharmacist before taking this product.

Ask a doctor or pharmacist before use if you are taking sedatives or tranquilizers.

Ask your doctor before use if you have

- heart disease
- diabetes
- high blood pressure
- thyroid disease
- glaucoma
- trouble urinating due to enlarged prostrate gland
- cough that occurs with to much phlegm (mucus)
- chronic cough that lasts such as occurs with smoking, asthma, chronic bronchitis, or emphysema

When using this product

- do not exceed recommended dosage

- may cause excitability especially in children
- may cause drowsiness: alcohol, sedatives,tranquilizers may increase the drowsiness effect
- avoid alcoholic beverages while taking this product
- use caution when driving a motor vehicle or operating machinery

Stop use and ask a doctor if

- you get nervous, dizzy, or sleepless
- symptoms do not improve within 7 days, tend to recur or are accompanied by fever and rash or persistent headache. These may be symptoms of a serious condition.

PREGNANCY OR BREAST FEEDING

If pregnant or breast-feeding, ask a health professional before use.

KEEP OUT OF REACH OF CHILDREN

Keep out of the reach of children. In case of overdose, get medical help or contact a Poison Control Center right away.

PURPOSE

Uses temporarily relieves these symptoms due to cold, hay fever or other upper respiratory allergies

- runny nose, sneezing, itching of the nose or throat, and itchy watery eyes
- cough due to minor throat and bronchial irritation
- nasal congestion

Questions? Reports of serious side effects
associated with use of the product call 787-832-6645.